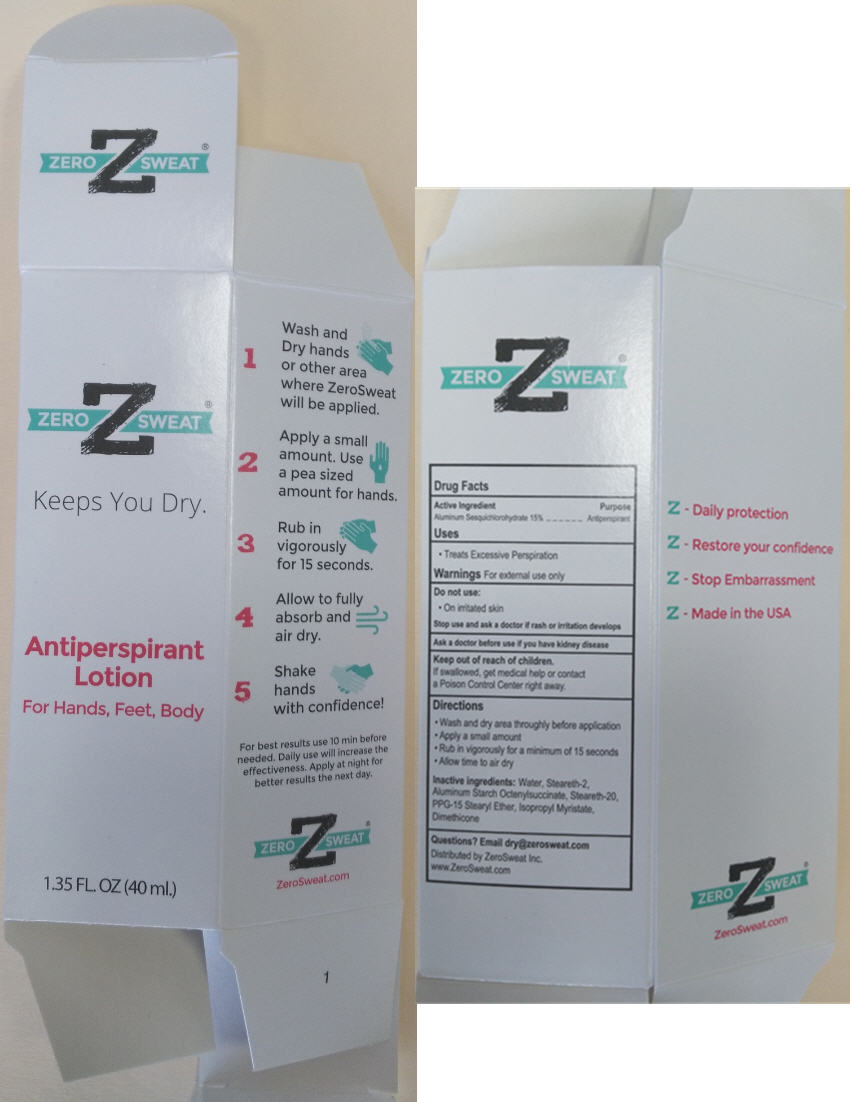 DRUG LABEL: Antiperspirant for Hands Feet Body 
NDC: 55726-293 | Form: LOTION
Manufacturer: Zero Sweat Inc.
Category: otc | Type: HUMAN OTC DRUG LABEL
Date: 20200110

ACTIVE INGREDIENTS: Aluminum Sesquichlorohydrate 150 mg/1 mL
INACTIVE INGREDIENTS: Water; Steareth-2; Aluminum starch Octenylsuccinate; Steareth-20; PPG-15 Stearyl Ether; Isopropyl Myristate; Dimethicone

Antiperspirant Lotion for Hands Feet Body
Zero Sweat®

Drug Facts

Active Ingredient

Aluminum Sesquichlorohydrate

Purpose

Antiperspirant

Uses

- Treats Excessive Perspiration

Warnings

For external use only

Do Not Use

on irritated skin

- On irritated skin

Stop use and ask a doctor if rash or irritation develops

Ask a doctor before use if you have kidney disease

Keep out of reach of children.

If swallowed, get medical help or contact a Poison Control Center right away.

Directions

- Wash and dry area thoroughly before application
- Apply a small amount
- Rub in vigorously for a minimum of 15
- Allow time to air dry

Inactive ingredients

Water,Steareth-2, Aluminum Starch Octenyl Succinate, Steareth-20, PPG-15 Stearyl Ether, Isopropyl Myristate, Dimethicone

Questions?

Email dry@zerosweat.com

Distributed by ZeroSweat Inc.

www.ZeroSweat.com

PRINCIPAL DISPLAY PANEL - 40 ml Tube Box

ZERO Z SWEAT®

Keeps You Dry.

Antiperspirant
Lotion

For Hands, Feet, Body

1.35 FL. OZ. (40 ml.)